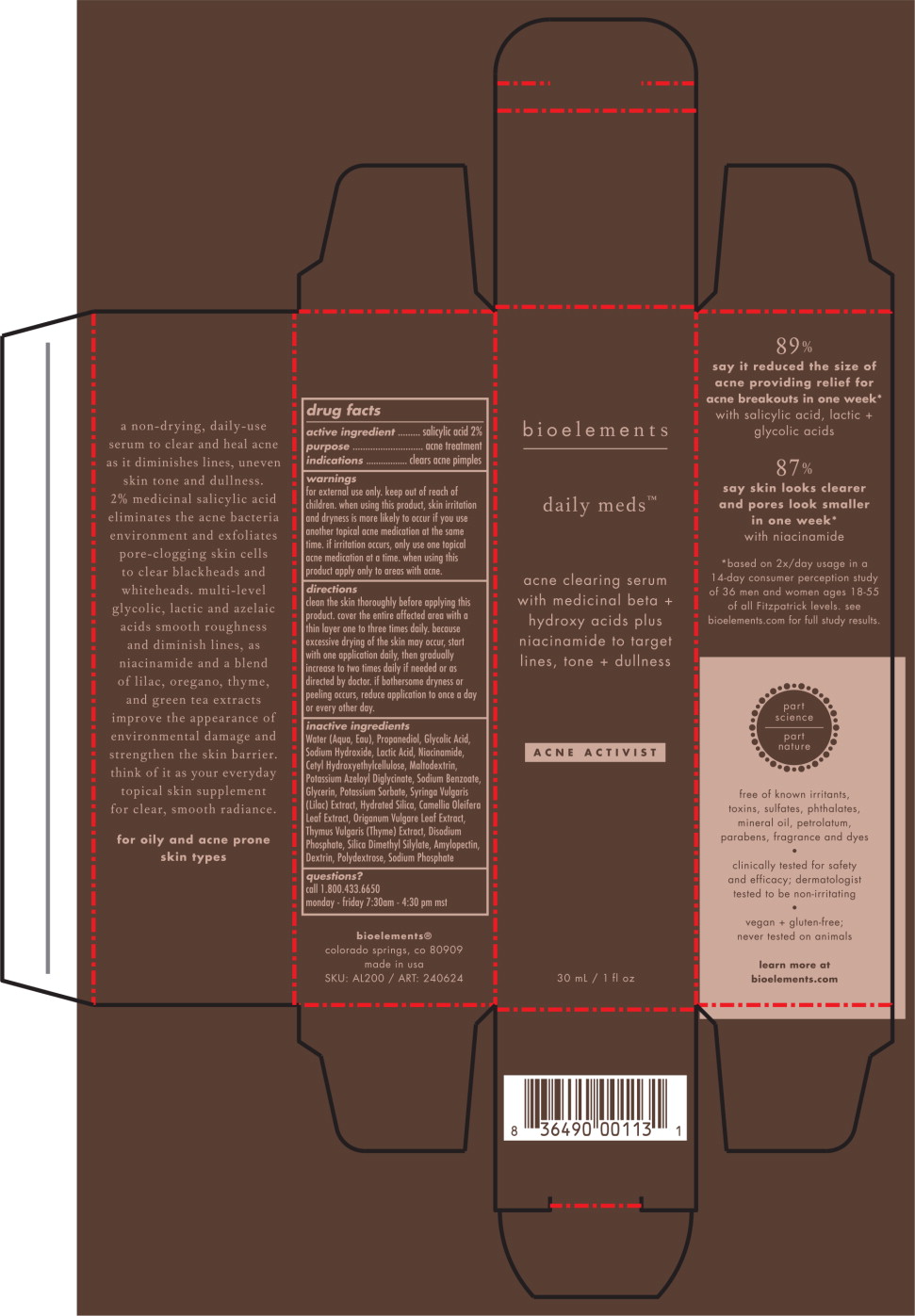 DRUG LABEL: Daily Meds
NDC: 49825-100 | Form: LOTION
Manufacturer: Bioelements, Inc.
Category: otc | Type: HUMAN OTC DRUG LABEL
Date: 20251114

ACTIVE INGREDIENTS: SALICYLIC ACID 20 mg/1 mL
INACTIVE INGREDIENTS: WATER; PROPANEDIOL; GLYCOLIC ACID; SODIUM HYDROXIDE; LACTIC ACID, UNSPECIFIED FORM; NIACINAMIDE; CETYL HYDROXYETHYLCELLULOSE (350000 MW); MALTODEXTRIN; POTASSIUM AZELOYL DIGLYCINATE; SODIUM BENZOATE; GLYCERIN; POTASSIUM SORBATE; SYRINGA VULGARIS FLOWER; HYDRATED SILICA; CAMELLIA OLEIFERA LEAF; OREGANO; THYME; SODIUM PHOSPHATE, DIBASIC, ANHYDROUS; SILICA DIMETHYL SILYLATE; AMYLOPECTIN, UNSPECIFIED SOURCE; DEXTRIN, CORN; POLYDEXTROSE; SODIUM PHOSPHATE

Daily Meds

active ingredient

salicylic acid 2%

purpose

acne treatment

indications

clears acne pimples

warnings

for external use only.

keep out of reach of children,

when using this product, skin irritation and dryness is more likely to occur if you use another topical acne medication at the same time. if irritation occurs, only use one topical acne medication at a time. when using this product apply only to areas with acne.

directions

clean the skin thoroughly before applying this product. cover the entire affected area with a thin layer one to three times daily. because excessive drying of the skin may occur, start with one application daily, then gradually increase to two times daily if needed or as directed by doctor. if bothersome dryness or peeling occurs, reduce application to once a day or every other day.

inactive ingredients

Water (Aqua, Eau), Propanediol, Glycolic Acid, Sodium Hydroxide, Lactic Acid, Niacinamide, Cetyl Hydroxyethylcellulose, Maltodextrin, Potassium Azeloyl Diglycinate, Sodium Benzoate, Glycerin, Potassium Sorbate, Syringa Vulgaris (Lilac) Extract, Hydrated Silica, Camellia Oleifera Leaf Extract, Origanum Vulgare Leaf Extract, Thymus Vulgaris (Thyme) Extract, Disodium Phosphate, Silica Dimethyl Silylate, Amylopectin, Dextrin, Polydextrose, Sodium Phosphate

questions?

call 1.800.433.6650

monday - friday 7:30am - 4:30 pm mst

Principal Display Panel – 30 mL Carton Label

bioelements

daily meds™

acne clearing serum
with medicinal beta +
alpha hydroxy acids plus
niacinamide to target
lines, tone + dullness

ACNE ACTIVIST

30 mL / 1 fl oz